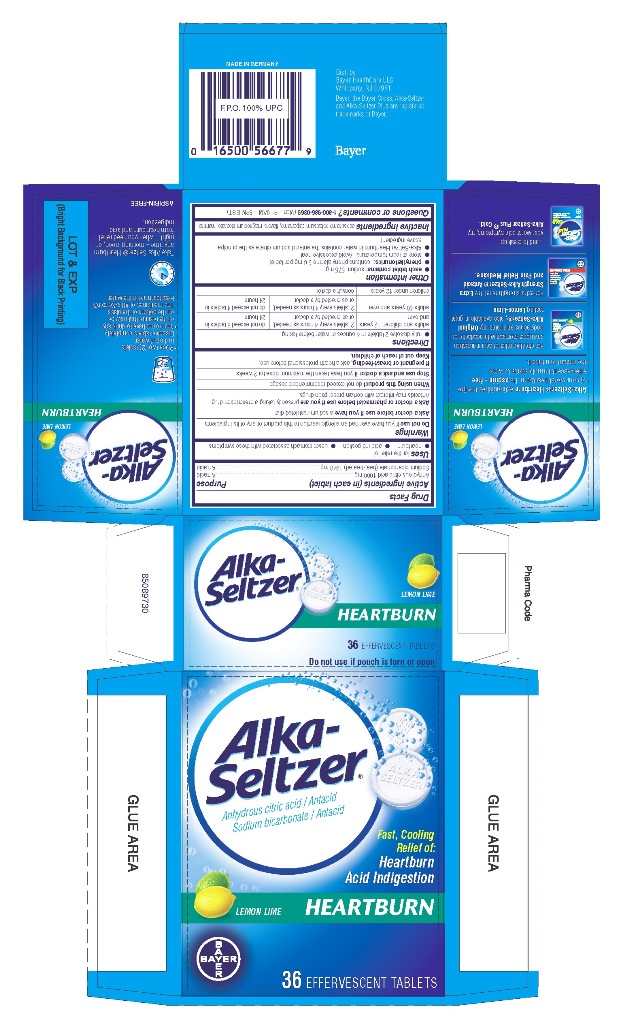 DRUG LABEL: Alka-Seltzer Heartburn
NDC: 0280-0047 | Form: TABLET, EFFERVESCENT
Manufacturer: Bayer HealthCare LLC.
Category: otc | Type: HUMAN OTC DRUG LABEL
Date: 20251204

ACTIVE INGREDIENTS: CITRIC ACID MONOHYDRATE 1000 mg/1 1; SODIUM BICARBONATE 1940 mg/1 1
INACTIVE INGREDIENTS: MAGNESIUM STEARATE; MANNITOL; ASPARTAME; ACESULFAME POTASSIUM

Alka-Seltzer Heartburn Effervescent Tablets

Active ingredients (in each tablet)

Anhydrous citric acid 1000 mg

Sodium bicarbonate (heat-treated) 1940 mg

Purpose

Active ingredients (in each tablet)...................................................................................Purpose
Anhydrous citric acid 1000 mg....................................................................................... Antacid
Sodium bicarbonate (heat-treated) 1940 mg ..............................................................Antacid

Uses

for the relief of

- heartburn
- acid indigestion
- upset stomach associated with these symptoms

Warnings

Do not use if you have ever had an allergic reaction to this product or any of its ingredients

Ask a doctor before use if you have a sodium-restricted diet

Ask a doctor or pharmacist before use if you are presently taking a prescription drug.
Antacids may interact with certain prescription drugs.

When using this product do not exceed recommended dosage

Stop use and ask a doctor if you have taken the maximum dose for 2 weeks

If pregnant or breast-feeding, ask a health professional before use.
Keep out of reach of children.

Keep out of reach of children

Directions

- fully dissolve 2 tablets in 4 ounces of water before taking
  adults and children 12 years and over | 2 tablets every 4 hours as needed, or as directed by a doctor | do not exceed 8 tablets in 24 hours
  adults 60 years and over | 2 tablets every 4 hours as needed, or as directed by a doctor | do not exceed 4 tablets in 24 hours
  children under 12 years | consult a doctor

Other information

- each tablet contains: sodium 575 mg
- phenylketonurics: contains phenylalanine 5.6 mg per tablet
- store at room temperature. Avoid excessive heat.
- Alka-Seltzer Heartburn in water contains the antacid sodium citrate as the principal
  active ingredient

Inactive ingredients

acesulfame potassium, aspartame, flavors, magnesium stearate, mannitol

Questions or comments? 1-800-986-0369 (Mon – Fri 9AM – 5PM EST)